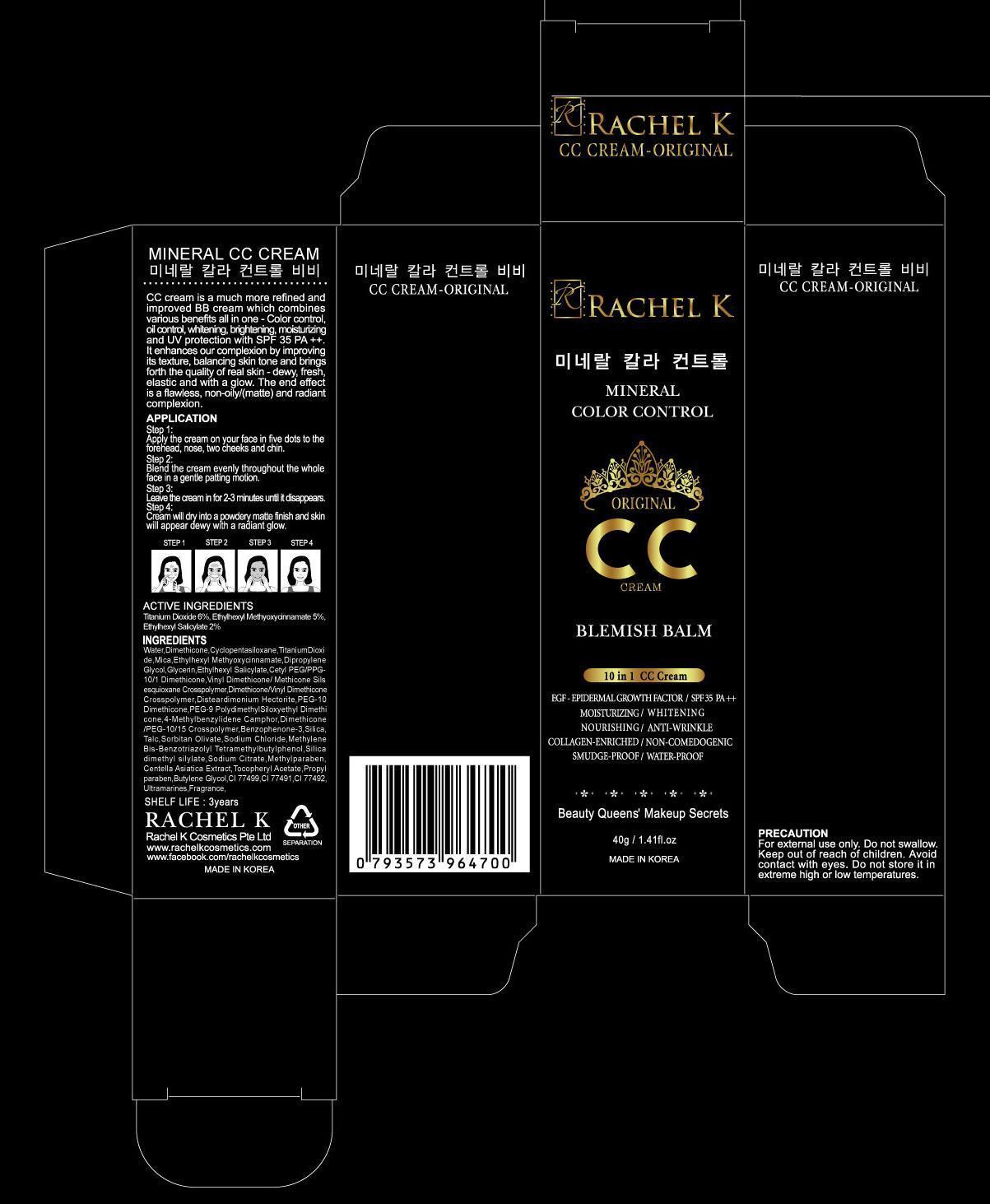 DRUG LABEL: RACHEL K MINERAL CC
NDC: 53241-010 | Form: CREAM
Manufacturer: RACHEL K COSMETICS PTE. LTD.
Category: otc | Type: HUMAN OTC DRUG LABEL
Date: 20120920

ACTIVE INGREDIENTS: TITANIUM DIOXIDE 2.4 g/40 g; OCTINOXATE 2 g/40 g; OCTISALATE 0.8 g/40 g
INACTIVE INGREDIENTS: WATER; DIMETHICONE; CYCLOMETHICONE 5; GLYCERIN

ACTIVE INGREDIENT

Active ingredients: TITANIUM DIOXIDE 6%, ETHYLHEXYL METHOXYCINNAMATE 5%, ETHYLHEXYL SALICYLATE 2%

INACTIVE INGREDIENT

Inactive ingredients:
Water, Dimethicone, Cyclopentasiloxane, Mica, Dipropylene Glycol, Glycerin, Cetyl PEG/PPG-10/1 Dimethicone, Vinyl Dimethicone/ Methicone Silsesquioxane Crosspolymer, Dimethicone/Vinyl Dimethicone Crosspolymer, Disteardimonium Hectorite, PEG-10 Dimethicone, PEG-9 PolydimethylSiloxyethyl Dimethicone, 4-Methylbenzylidene Camphor, Dimethicone/PEG-10/15 Crosspolymer, Benzophenone-3, Silica, Talc, Sorbitan Olivate, Sodium Chloride, Methylene Bis-Benzotriazolyl Tetramethylbutylphenol, Silica dimethyl silylate, Sodium Citrate, Methylparaben, Centella Asiatica Extract, Tocopheryl Acetate, Propylparaben, Butylene Glycol, Sodium Hyaluronate, Arbutin, Adenosine, Human Oligopeptide-1, Ultramarines, Fragrance

PURPOSE

Purpose: Sunscreen

WARNINGS

PRECAUTION:
For external use only.
Do not swallow.
Keep out of reach of children.
Avoid contact with eyes.
Do not store it in extreme high or low temperatures

KEEP OUT OF REACH OF CHILDREN

INDICATIONS AND USAGE

APPLICATION:
1. Apply the cream on your face in five dots to the forehead, nose, two cheeks and chin.
2. Blend the cream evenly throughout the whole face in a gentle patting motion.
3. Leave the cream in for 2-3 minutes until it disappears.
4. Cream will dry into a powdery matte finish and skin will appear dewy with a radiant glow.

DOSAGE AND ADMINISTRATION

APPLICATION:
1. Apply the cream on your face in five dots to the forehead, nose, two cheeks and chin.
2. Blend the cream evenly throughout the whole face in a gentle patting motion.
3. Leave the cream in for 2-3 minutes until it disappears.
4. Cream will dry into a powdery matte finish and skin will appear dewy with a radiant glow.